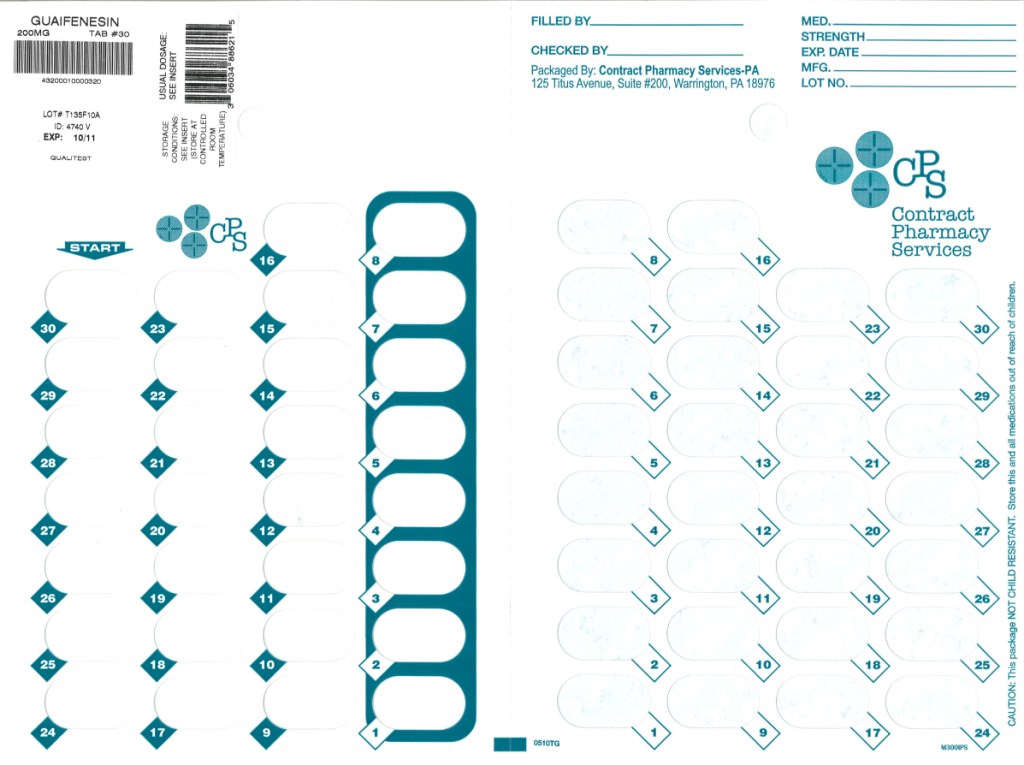 DRUG LABEL: Guaifenesin
NDC: 67046-250 | Form: TABLET
Manufacturer: Contract Pharmacy Services-PA
Category: prescription | Type: HUMAN PRESCRIPTION DRUG LABEL
Date: 20101006

ACTIVE INGREDIENTS: GUAIFENESIN 200 mg/1 1
INACTIVE INGREDIENTS: CROSPOVIDONE; D&C RED NO. 30; MAGNESIUM STEARATE; CELLULOSE, MICROCRYSTALLINE; SILICON DIOXIDE; SODIUM STARCH GLYCOLATE TYPE A POTATO; STEARIC ACID

Professional Labeling Information and Directions for Use
These products labeled for sale on prescription only.
Guaifenesin Tablets

DESCRIPTION

Guaifenesin (glyceryl guaiacolate) has the chemical name 3-(2-methoxyphenoxy)-1,2-propanediol. Its molecular formula is C10H14O4 with a molecular weight of 198.21. It is a white or slightly gray crystalline substance with a slightly bitter aromatic taste. One gram dissolves in 20 mL water at 25°C; it is freely soluble in ethanol. Guaifenesin is readily absorbed from the GI tract and is rapidly metabolized and excreted in the urine. Guaifenesin has a plasma half-life of one hour. The major urinary metabolite is β-(2-methoxyphenoxy) lactic acid.

Guaifenesin is an expectorant available for oral administration as:

Tablets — each containing 200 mg guaifenesin, USP.

Other ingredients: crospovidone, D&C red #30 aluminum lake, magnesium stearate, microcrystalline cellulose, polysaccharides, pregelatinized starch, silicon dioxide, sodium starch glycolate, and stearic acid.

CLINICAL PHARMACOLOGY

Guaifenesin is an expectorant, the action of which promotes or facilitates the removal of secretions from the respiratory tract. By increasing sputum volume and making sputum less viscous, guaifenesin facilitates expectoration of retained secretions.

INDICATIONS AND USAGE

Helps loosen phlegm (mucus) and thin bronchial secretions to rid the bronchial passageways of bothersome mucus, drain bronchial tubes and make coughs more productive. Helps loosen phlegm and thin bronchial secretions in patients with stable chronic bronchitis.

CONTRAINDICATIONS

Hypersensitivity to any of the ingredients.

PRECAUTIONS

CARCINOGENESIS AND MUTAGENESIS AND IMPAIRMENT OF FERTILITY

Carcinogenesis, Mutagenesis, Impairment of Fertility: Animal studies to assess the long-term carcinogenic and mutagenic potential or the effect on fertility in animals or humans have not been performed.

Pregnancy:

TERATOGENIC EFFECTS

Teratogenic Effects—Pregnancy Category C: Animal reproduction studies have not been conducted. Safe use in pregnancy has not been established relative to possible adverse effects on fetal development. Therefore, these products should not be used in pregnant patients unless, in the judgment of the physician, the potential benefits outweigh possible hazards.

NURSING MOTHERS

Nursing Mothers: It is not known whether guaifenesin is excreted in human milk. Because many drugs are excreted in human milk, caution should be exercised when these products are administered to a nursing woman and a decision should be made whether to discontinue nursing or to discontinue the drug, taking into account the importance of the drug to the mother.

LABORATORY TESTS

Laboratory Test Interactions: Guaifenesin or its metabolites may cause color interference with the VMA (vanillylmandelic acid) test for catechols. It may also falsely elevate the level of urinary 5-HIAA (5-hydroxyindoleacetic acid) in certain serotonin metabolite chemical tests because of color interference.

ADVERSE REACTIONS

To report SUSPECTED ADVERSE REACTIONS, contact FDA at 1-800-FDA-1088 or www.fda.gov/medwatch.

Guaifenesin is well tolerated and has a wide margin of safety. Side effects have been generally mild and infrequent. Nausea and vomiting are the side effects that occur most commonly. Dizziness, headache, and rash (including urticaria) have been reported rarely.

OVERDOSAGE

In massive overdosage the stomach should be emptied (emesis and/or gastric lavage) and further absorption prevented. Treatment is symptomatic and supportive.

The acute toxicity of guaifenesin is low and overdosage is unlikely to produce serious toxic effects. In laboratory animals no toxicity resulted when guaifenesin was administered by stomach tube in doses up to 5 grams/kg.

DOSAGE AND ADMINISTRATION

Adults and children 12 years of age and older: One to 2 tablets (200 mg to 400 mg) every four hours, not to exceed 2400 mg (12 tablets) in 24 hours.

PATIENTS SHOULD BE ADVISED TO KEEP THESE AND ALL DRUGS OUT OF THE REACH OF CHILDREN AND TO SEEK PROFESSIONAL ASSISTANCE OR CONTACT A POISON CONTROL CENTER IMMEDIATELY IN CASE OF ACCIDENTAL OVERDOSE.

HOW SUPPLIED

Guaifenesin

Tablets — Each round, scored, rose-colored tablet contains 200 mg guaifenesin USP—available in blisters of 30 (NDC 67046-250-30)

STORAGE AND HANDLING

STORAGE — Store at controlled room temperature 20°-25°C (68°-77°F). Protect tablets from moisture. Keep bottle tightly closed.

To report SUSPECTED ADVERSE REACTIONS, contact FDA at 1-800-FDA-1088 or www.fda.gov/medwatch.

Qualitest PHARMACEUTICALS®
Huntsville, AL 35811
8180142 Rev 5/08

PACKAGE LABEL

Blister of 30 Tablets